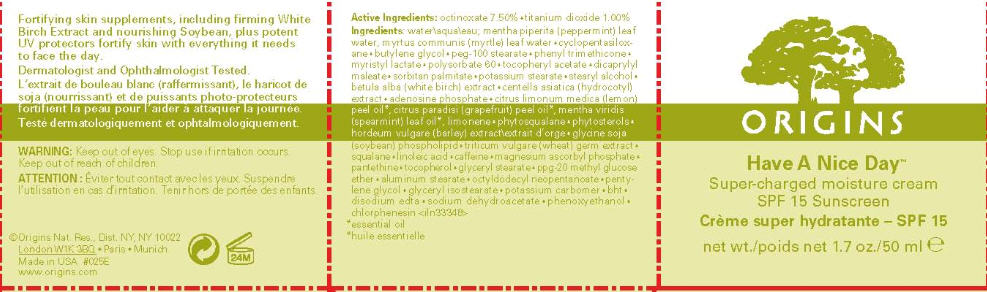 DRUG LABEL: HAVE A NICE DAY 
NDC: 59427-783 | Form: CREAM
Manufacturer: ORIGINS NATURAL RESOURCES INC.
Category: otc | Type: HUMAN OTC DRUG LABEL
Date: 20110908

ACTIVE INGREDIENTS: octinoxate 7.5 mL/100 mL; titanium dioxide 1 mL/100 mL
INACTIVE INGREDIENTS: water; peppermint oil; myrtle leaf oil; cyclomethicone 5; butylene glycol; peg-100 stearate; phenyl trimethicone; myristyl lactate; polysorbate 60; ALPHA-TOCOPHEROL ACETATE; dioctyl maleate; sorbitan monopalmitate; potassium stearate; stearyl alcohol; betula pubescens bark; centella asiatica leaf; adenosine phosphate; lemon oil; grapefruit oil; spearmint oil; barley; soybean; wheat germ; squalane; linoleic acid; caffeine; magnesium ascorbyl phosphate; pantethine; tocopherol; glyceryl monostearate; aluminum stearate; octyldodecyl neopentanoate; pentylene glycol; glyceryl isostearate; butylated hydroxytoluene; edetate disodium; sodium dehydroacetate; phenoxyethanol; chlorphenesin

ORIGINS
Have A Nice Day™
Super-charged moisture cream
SPF 15 Sunscreen

Active Ingredients

octinoxate 7.50% • titanium dioxide 1.00%

Ingredients

water\aqua\eau; mentha piperita (peppermint) leaf water, myrtus communis (myrtle) leaf water • cyclopentasiloxane • butylene glycol • peg-100 stearate • phenyl trim ethicone • myristyl lactate • polysorbate 60 • tocopheryl acetate • dicaprylyl maleate • sorbitan palmitate • potassium stearate • stearyl alcohol • betula alba (white birch) extract • centella asiatica (hydrocotyl) extract • adenosine phosphate • citrus limonum medica (lemon) peel oil [essential oil] , citrus paradisi (grapefruit) peel oil, mentha viridis (spearmint) leaf oil, limonene • phytosqualane • phytosterols • hordeum vulgare (barley) extract\extrait d'orge • glycine soja (soybean) phospholipid • triticum vulgare (wheat) germ extract • squalane • linoleic acid • caffeine • magnesium ascorbyl phosphate • pantethine • tocopherol • glyceryl stearate • ppg-20 methyl glucose ether • aluminum stearate • octyldodecyl neopentanoate • pentylene glycol • glyceryl isostearate • potassium carbomer • bht • disodium edta • sodium dehydroacetate • phenoxyethanol • chlorphenesin <iln33348>

PURPOSE

Fortifying skin supplements, including firming White Birch Extract and nourishing Soybean, plus potent UV protectors fortify skin with everything it needs to face the day.

WARNING

DO NOT USE

Keep out of eyes.

Stop use if irritation occurs.

Keep out of reach of children.

©Origins Nat. Res., Dist. NY, NY 10022

PRINCIPAL DISPLAY PANEL - 50 ml Jar Carton

ORIGINS

Have A Nice Day™

Super-charged moisture cream
SPF 15 Sunscreen

net wt. 1.7 oz./50 ml e